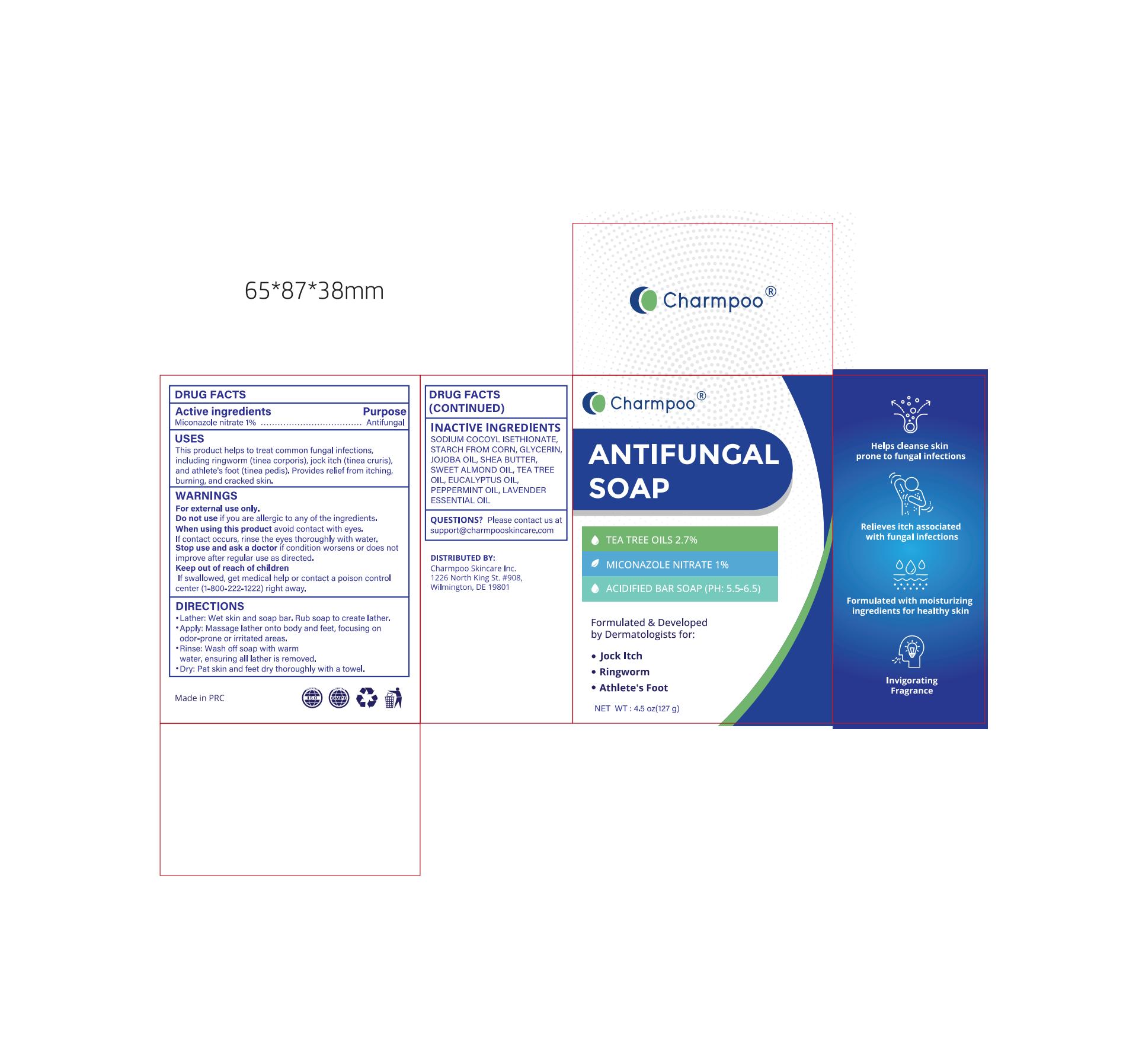 DRUG LABEL: Charmpoo  ANTIFUNCAL
NDC: 84010-064 | Form: SOAP
Manufacturer: Jiangxi Hemei Pharmaceutical Co., Ltd
Category: otc | Type: HUMAN OTC DRUG LABEL
Date: 20250114

ACTIVE INGREDIENTS: MICONAZOLE NITRATE 1 g/100 g
INACTIVE INGREDIENTS: STARCH, CORN; JOJOBA OIL; SODIUM COCOYL ISETHIONATE; GLYCERIN; SHEA BUTTER; EUCALYPTUS OIL; LAVENDER OIL; TEA TREE OIL; PRUNUS AMYGDALUS DULCIS (SWEET ALMOND) OIL; PEPPERMINT OIL

84010-064 Completed

Active Ingredient

Miconazole nitrate 1%

Purpose

Antifungal

Use

This product helps to treat common fungal infections,including ringworm (tinea corporis), jock itch (tinea cruris),and athlete's foot (tinea pedis). Provides relief from itching,burning, and cracked skin.

Warnings

For external use only.

Do not use if you are allergic to any of the ingredients.

When Using

When using this product avoid contact with eyes.If contact occurs, rinse the eyes thoroughly with water.

Stop Use

Stop use and ask a doctor if condition worsens or does not improve after regular use as directed.

Ask Doctor

Stop use and ask a doctor if condition worsens or does not improve after regular use as directed.

Keep Oot Of Reach Of Children

If swallowed, get medical help or contact a poison control center (1-800-222-1222)right away.

Directions

·Lather: Wet skin and soap bar. Rub soap to create lather.
·Apply: Massage lather onto body and feet, focusing on odor-prone or irritated areas.
·Rinse: Wash off soap with warm
water, ensuring al lather is removed.
·Dry: Pat skin and feet dry thoroughly with a towel.

Inactive ingredients

SODIUM COCOYL ISETHIONATE,STARCH FROM CORN, GLYCERIN，JOJOBA OIL, SHEA BUTTER,SWEET ALMOND OIL, TEA TREE OIL, EUCALYPTUS OIL,PEPPERMINT OIL, LAVENDER ESSENTIAL OIL

Questions

Please contact us at support@charmpooskincare.com